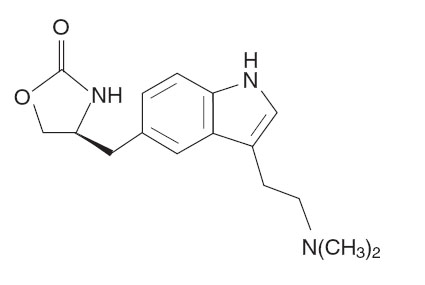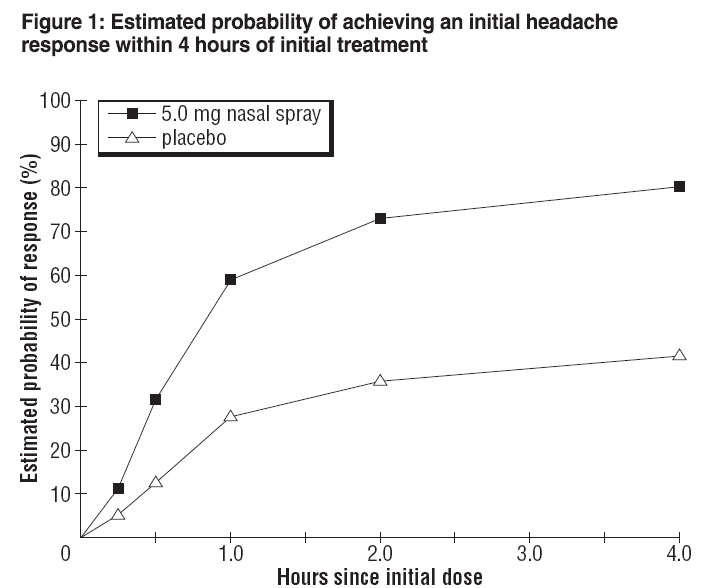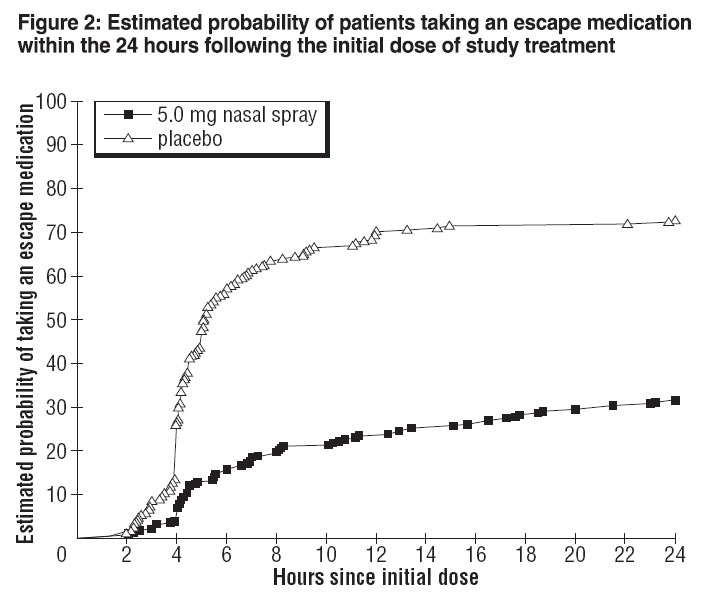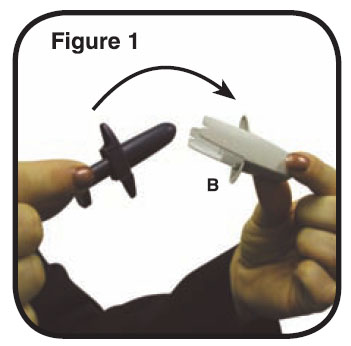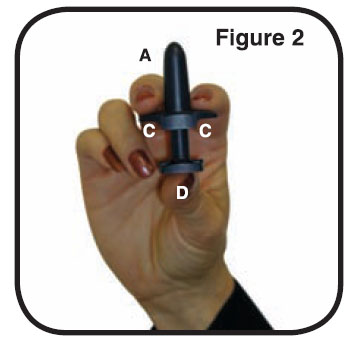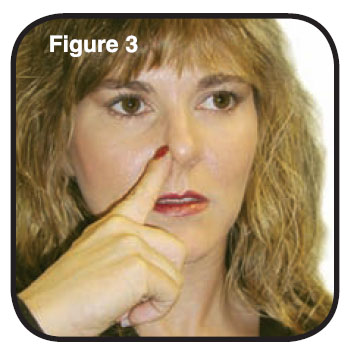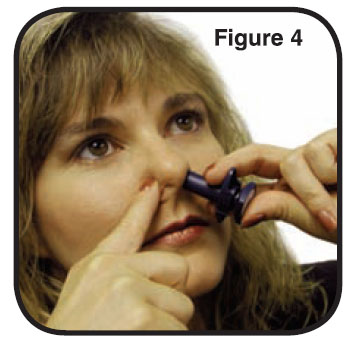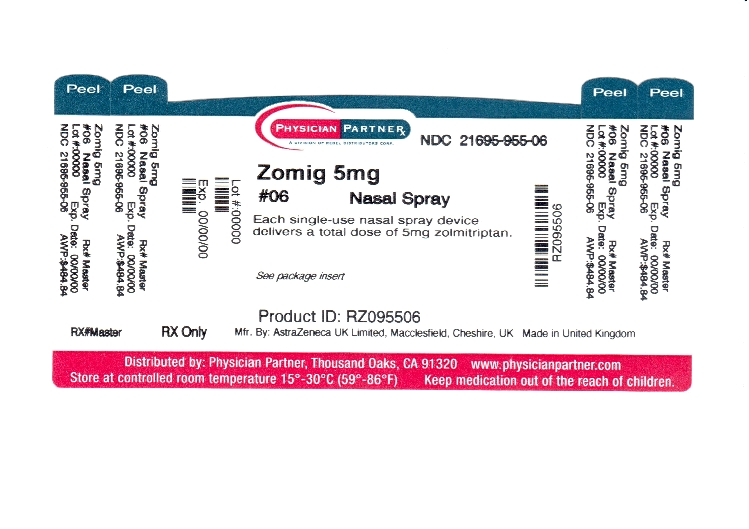 DRUG LABEL: ZOMIG
NDC: 21695-955 | Form: SPRAY, METERED
Manufacturer: Rebel Distributors Corp
Category: prescription | Type: HUMAN PRESCRIPTION DRUG LABEL
Date: 20110913

ACTIVE INGREDIENTS: ZOLMITRIPTAN 5 mg/1 1
INACTIVE INGREDIENTS: CITRIC ACID ANHYDROUS; SODIUM PHOSPHATE, DIBASIC; WATER; NITROGEN

HIGHLIGHTS OF PRESCRIBING INFORMATION

These highlights do not include all the information needed to use ZOMIG NASAL SPRAY. See full prescribing information for
ZOMIG® (zolmitriptan) NASAL SPRAY
INITIAL U.S. APPROVAL: 1997

RECENT MAJOR CHANGES

Warning and Precautions, serotonin syndrome (5.5) 10/2008

Drug Interactions, serotonin syndrome (7.5) 10/2008

Use in Specific Populations, pediatric use (8.4) 10/2008

1 INDICATIONS AND USAGE

ZOMIG Nasal Spray is a 5HT1B/1D receptor agonist (triptan) indicated for:

Acute treatment of migraine with or without aura in adults (1)

Important limitations:

Use only after a clear diagnosis of migraine has been established (1.2)
Not intended for the prophylactic therapy of migraine (1.2)
Not indicated for the treatment of cluster headache (1.2)

2 DOSAGE AND ADMINISTRATION

Single 5 mg dose; may repeat after 2 hours if needed; not to exceed 10 mg in any 24-hour period; benefit of a second dose not established (2)

3 DOSAGE FORMS AND STRENGTHS

Nasal Spray: 5 mg (3)

4 CONTRAINDICATIONS

Ischemic heart disease, coronary artery vasospasm, or other significant underlying cardiovascular disease (4.1)
Cerebrovascular syndromes (e.g. history of stroke or TIA) (4.2)
Peripheral Vascular Disease (including ischemic bowel disease) (4.3)
Uncontrolled hypertension (4.4)
Do not use ZOMIG within 24 hours of another 5-HT1 agonist, ergotamine-containing or ergot-type medication (4.5)
Hemiplegic or basilar migraine (4.6)
Do not use ZOMIG within 2 weeks of an MAO-A inhibitor (4.7)
Hypersensitivity to ZOMIG (4.8)

5 WARNINGS AND PRECAUTIONS

Serious adverse cardiac events, including acute myocardial infarction, and life-threatening disturbances of cardiac rhythm (5.1)
It is strongly recommended that ZOMIG not be given to patients in whom unrecognized coronary artery disease (CAD) is predicted by the presence of risk factors. In very rare cases, serious cardiovascular events have been reported in association with ZOMIG in the absence of known cardiovascular disease. If ZOMIG is considered, patients should first have a cardiovascular evaluation. If the evaluation is satisfactory, first dose should take place in a physician’s office setting (5.1)
Sensations of pain, tightness, pressure and heaviness in the chest, throat, neck and jaw: generally not associated with myocardial ischemia, but patients with signs or symptoms suggestive of angina should be evaluated for the presence of CAD (5.2)
Cerebrovascular events, some fatal (5.3)
Gastrointestinal ischemic events and peripheral vasospastic reactions (e.g. Raynaud’s syndrome) (5.4)
Patients with symptomatic Wolff-Parkinson-White syndrome or arrhythmias associated with other cardiac accessory conduction pathways should not receive ZOMIG (5.1)
Potentially life-threatening serotonin syndrome, particularly in combination with SSRIs or SNRIs. Monitor patients carefully if concomitant treatment is clinically warranted (5.5, 7.6)
Increase in blood pressure, very rarely associated with significant clinical events (4.4, 5.6)

6 ADVERSE REACTIONS

In controlled studies the most common adverse reactions (≥ 2% and > placebo) were: unusual taste, paresthesia, hyperesthesia, nausea, pain location specified, pain throat, somnolence, asthenia, disorder/discomfort of nasal cavity, dry mouth, tightness throat (6.1)

To report SUSPECTED ADVERSE REACTIONS, contact AstraZeneca at 1-800-236-9933 or FDA at 1-800-FDA-1088 or www.fda.gov/medwatch

7 DRUG INTERACTIONS

Ergot-type or ergotamine-containing medications other 5HT1 agonists, and ZOMIG: do not use within 24 hours of each other (4.5, 7.1, 7.3)
Do not use ZOMIG within 2 weeks of an MAO-A inhibitor (4.7, 7.2)
Cimetidine: half-life and AUC of zolmitriptan doubled (7.4)
SSRI or SNRI: life-threatening serotonin syndrome reported during combined use with triptans (5.5, 7.5)

8 USE IN SPECIFIC POPULATIONS

Pregnancy: Based on animal data, may cause fetal harm. Use ZOMIG during pregnancy only if the potential benefit justifies the potential risk to the fetus (8.1)
Nursing Mothers: Use with caution while nursing, as it is not known if ZOMIG is excreted in human milk. Zolmitriptan has been detected in rat milk at levels equal to or greater than those in maternal plasma (8.3)
Pediatric Use: Efficacy not established in a study in patients 12-17 years. Adverse reactions similar in nature and frequency to adults. Not studied in patients under 12 years (8.4)
Geriatric Use: Safety and effectiveness in patients over 65 not established (8.5, 12.3)
Hepatic Impairment: Decreased clearance of zolmitriptan and significant elevation in blood pressure observed. Use doses < 2.5 mg of an oral formulation, with blood pressure monitoring (2.2, 8.6, 12.3)

FULL PRESCRIBING INFORMATION

1 INDICATIONS AND USAGE

1.1 Acute Treatment of Migraine Attacks

ZOMIG Nasal Spray is indicated for the acute treatment of migraine with or without aura in adults.

1.2 Important Limitations

ZOMIG should only be used where a clear diagnosis of migraine has been established. If a patient has no response for the first migraine attack treated with ZOMIG, the diagnosis of migraine should be reconsidered before ZOMIG is administered to treat any subsequent attacks.

ZOMIG is not intended for the prophylactic therapy of migraine or for use in the management of hemiplegic or basilar migraine [see Contraindications (4.6)].

Safety and effectiveness of ZOMIG have not been established for cluster headache, which is present in an older, predominantly male population.

2 DOSAGE AND ADMINISTRATION

2.1 Acute Treatment of Migraine Attacks

Administer one dose of ZOMIG Nasal Spray 5 mg for the treatment of acute migraine. If the headache returns, the dose may be repeated after 2 hours. The effectiveness of a second dose has not been established in placebo-controlled trials. The maximum daily dose should not exceed 10 mg in any 24-hour period.

In controlled clinical trials, single doses of 5 mg of zolmitriptan nasal spray were administered into one nostril and were effective for the treatment of acute migraines in adults.

Individuals may vary in response to ZOMIG Nasal Spray. The pharmacokinetics of a 5 mg nasal spray dose is similar to the 5 mg oral formulations. Doses lower than 5 mg can only be achieved through the use of an oral formulation. The choice of dose, and route of administration should therefore be made on an individual basis.

The safety of treating an average of more than four headaches in a 30-day period has not been established.

2.2 Hepatic Impairment

Patients with moderate to severe hepatic impairment have decreased clearance of zolmitriptan and significant elevation in blood pressure was observed in some patients. Use of doses less than 2.5mg of an alternate formulation with blood pressure monitoring is recommended [see Clinical Pharmacology (12.3) and Warnings and Precautions (5.6)].

3 DOSAGE FORMS AND STRENGTHS

Nasal Spray 5 mg

4 CONTRAINDICATIONS

4.1 Ischemic or Vasospastic Coronary Artery Disease

ZOMIG should not be given to patients with ischemic heart disease (angina pectoris, history of myocardial infarction, or documented silent ischemia) or to patients who have symptoms or findings consistent with ischemic heart disease, coronary artery vasospasm, including Prinzmetal’s variant angina, or other significant underlying cardiovascular disease [see Warnings and Precautions (5.1)].

4.2 Cerebrovascular Syndromes

ZOMIG should not be given to patients with cerebrovascular syndromes including (but not limited to) stroke of any type as well as transient ischemic attacks. [see Warnings and Precautions (5.3)].

4.3 Peripheral Vascular Disease

ZOMIG should not be given to patients with peripheral vascular disease including (but not limited to) ischemic bowel disease [see Warnings and Precautions (5.4)].

4.4 Uncontrolled Hypertension

Because ZOMIG may increase blood pressure, it should not be given to patients with uncontrolled hypertension [see Warnings and Precautions (5.6)].

4.5 Use within 24 hours of treatment with another 5-HT1 agonist, or ergotamine containing medication, or ergot type medication

ZOMIG and any ergotamine-containing or ergot-type medication (such as dihydroergotamine or methysergide) should not be used within 24 hours of each other, nor should ZOMIG and another 5-HT1 agonist be used within 24 hours of each other [See Drug Interactions (7.1 and 7.3)].

4.6 Hemiplegic or Basilar Migraine

ZOMIG should not be administered to patients with hemiplegic or basilar migraine.

4.7 Administration of MAO-A inhibitors within 2 weeks

Concurrent administration of MAO-A inhibitors or use of zolmitriptan within 2 weeks of discontinuation of MAO-A inhibitor therapy is contraindicated [see Clinical Pharmacology (12.4) and Drug Interactions (7.2)].

4.8 Hypersensitivity to zolmitriptan

ZOMIG is contraindicated in patients who are hypersensitive to zolmitriptan or any of its inactive ingredients.

5 WARNINGS AND PRECAUTIONS

5.1 Risk of Myocardial Ischemia and/or Infarction and Other Adverse Cardiac Events

Cardiac Events and Fatalities with 5-HT1 Agonists

Serious adverse cardiac events, including acute myocardial infarction, have been reported within a few hours following administration of zolmitriptan. Life-threatening disturbances of cardiac rhythm, and death have been reported within a few hours following the administration of other 5-HT1 agonists. Considering the extent of use of 5-HT1 agonists in patients with migraine, the incidence of these events is extremely low.

ZOMIG can cause coronary artery vasospasm; at least one of these events occurred in a patient with no cardiac disease history and with documented absence of coronary artery disease. Because of the close proximity of the events to ZOMIG use, a causal relationship cannot be excluded. In the cases where there has been known underlying coronary artery disease, the relationship is uncertain. Patients who experience signs or symptoms suggestive of angina following dosing should be evaluated for the presence of CAD or a predisposition to Prinzmetal’s variant angina before receiving additional doses of medication, and should be monitored electrocardiographically if dosing is resumed and similar symptoms recur.

Patients with symptomatic Wolff-Parkinson-White syndrome or arrhythmias associated with other cardiac accessory conduction pathway disorders should not receive ZOMIG.

Premarketing experience with zolmitriptan

Among the more than 2,500 patients with migraine who participated in premarketing controlled clinical trials of ZOMIG Tablets, no deaths or serious cardiac events were reported. In a premarketing controlled clinical trial of ZOMIG Nasal Spray, more than 1,300 patients participated and there were no deaths or serious cardiac events to report.

Postmarketing experience with zolmitriptan

Serious cardiovascular events have been reported in association with the use of ZOMIG Tablets, and in very rare cases, these events have occurred in the absence of known cardiovascular disease. The uncontrolled nature of postmarketing surveillance, however, makes it impossible to determine definitively the proportion of the reported cases that were actually caused by zolmitriptan or to reliably assess causation in individual cases.

Patients with documented coronary artery disease

Because of the potential of this class of compound (5-HT1 agonists) to cause coronary vasospasm, ZOMIG should not be given to patients with documented ischemic or vasospastic coronary artery disease [see Contraindications (4.1)].

Patients with risk factors for CAD

It is strongly recommended that zolmitriptan not be given to patients in whom unrecognized coronary artery disease (CAD) is predicted by the presence of risk factors (eg, hypertension, hypercholesterolemia, smoker, obesity, diabetes, strong family history of CAD, female with surgical or physiological menopause, or male over 40 years of age) unless a cardiovascular evaluation provides satisfactory clinical evidence that the patient is reasonably free of coronary artery and ischemic myocardial disease or other significant underlying cardiovascular disease. The sensitivity of cardiac diagnostic procedures to detect cardiovascular disease or predisposition to coronary artery vasospasm is modest, at best. If, during the cardiovascular evaluation, the patient’s medical history, electrocardiographic or other investigations reveal findings indicative of, or consistent with, coronary artery vasospasm or myocardial ischemia, zolmitriptan should not be administered [see Contraindications (4.1)].

For patients with risk factors predictive of CAD, who are determined to have a satisfactory cardiovascular evaluation, it is strongly recommended that administration of the first dose of zolmitriptan take place in the setting of a physician’s office or similar medically staffed and equipped facility unless the patient has previously received zolmitriptan. Because cardiac ischemia can occur in the absence of clinical symptoms, consideration should be given to obtaining on the first occasion of use an electrocardiogram (ECG) during the interval immediately following ZOMIG, in these patients with risk factors.

It is recommended that patients who are intermittent long-term users of ZOMIG and who have or acquire risk factors predictive of CAD, as described above, undergo periodic interval cardiovascular evaluation as they continue to use ZOMIG.

The systematic approach described above is intended to reduce the likelihood that patients with unrecognized cardiovascular disease will be inadvertently exposed to zolmitriptan.

5.2 Sensations of pain, tightness, pressure in the chest and or throat, neck and jaw

As with other 5-HT1 agonists, sensations of tightness, pain, pressure, and heaviness in the precordium, throat, neck, and jaw have been reported after treatment with ZOMIG Tablets.

Because 5-HT1 agonists may cause coronary vasospasm, patients who experience signs or symptoms suggestive of angina following dosing should be evaluated for the presence of CAD or a predisposition to Prinzmetal’s variant angina before receiving additional doses of medication, and should be monitored electrocardiographically if dosing is resumed and similar symptoms occur. Patients shown to have CAD and those with Prinzmetal’s variant angina should not receive 5-HT1 agonists [see Contraindications (4.1)].

5.3 Cerebrovascular Events

Cerebral hemorrhage, subarachnoid hemorrhage, stroke, and other cerebrovascular events have been reported in patients treated with 5-HT1 agonists, and some have resulted in fatalities. In a number of cases, it appears possible that the cerebrovascular events were primary, the agonist having been administered in the incorrect belief that the symptoms experienced were a consequence of migraine, when they were not. As with other acute migraine therapies, before treating headaches in patients not previously diagnosed as migraineurs, and in migraineurs who present with atypical symptoms, care should be taken to exclude other potentially serious neurological conditions. It should be noted that patients with migraine may be at increased risk of certain cerebrovascular events (eg, stroke, hemorrhage, transient ischemic attack) [see Contraindications (4.2)].

5.4 Other Vasospasm-Related Events, including Peripheral Vascular Ischemia and Colonic Ischemia

5-HT1 agonists, including ZOMIG, may cause vasospastic reactions other than coronary artery vasospasm, such as peripheral and gastrointestinal vascular ischemia with abdominal pain and bloody diarrhea.

Very rare reports of transient and permanent blindness and significant partial vision loss have been reported with the use of 5-HT1 agonists. Visual disorders may also be part of a migraine attack.

Patients who experience other symptoms or signs suggestive of decreased arterial flow following the use of any 5-HT agonist, such as ischemic bowel syndrome or Raynaud’s syndrome, are candidates for further evaluation [see Contraindications (4.3)].

5.5 Serotonin Syndrome

The development of a potentially life-threatening serotonin syndrome may occur with triptans, including ZOMIG treatment, particularly during combined use with selective serotonin reuptake inhibitors (SSRIs) or serotonin norepinephrine reuptake inhibitors (SNRIs). If concomitant treatment with ZOMIG and an SSRI (e.g., fluoxetine, paroxetine, sertraline, fluvoxamine, citalopram, escitalopram) or SNRI (e.g., venlafaxine, duloxetine) is clinically warranted, careful observation of the patient is advised, particularly during treatment initiation and dose increases. Serotonin syndrome symptoms may include mental status changes (e.g., agitation, hallucinations, coma), autonomic instability (e.g., tachycardia, labile blood pressure, hyperthermia), neuromuscular aberrations (e.g., hyperreflexia, incoordination) and/or gastrointestinal symptoms (e.g., nausea, vomiting, diarrhea) [See Drug Interactions (7.5)].

5.6 Increase in Blood Pressure

As with other 5-HT1 agonists, significant elevations in systemic blood pressure have been reported on rare occasions with ZOMIG Tablet use, in patients with and without a history of hypertension; very rarely these increases in blood pressure have been associated with significant clinical events. Zolmitriptan is contraindicated in patients with uncontrolled hypertension. In volunteers, an increase of 1 and 5 mm Hg in the systolic and diastolic blood pressure, respectively, was seen at 5 mg. In the headache trials, vital signs were measured only in the small inpatient study and no effect on blood pressure was seen. In a study of patients with moderate to severe liver disease, 7 of 27 experienced 20 to 80 mm Hg elevations in systolic and/or diastolic blood pressure after a dose of 10 mg of zolmitriptan [see Contraindications (4.4)].

An 18% increase in mean pulmonary artery pressure was seen following dosing with another 5-HT1 agonist in a study evaluating subjects undergoing cardiac catheterization.

5.7 Binding to Melanin-Containing Tissues

When pigmented rats were given a single oral dose of 10 mg/kg of radiolabeled zolmitriptan, the radioactivity in the eye after 7 days, the latest time point examined, was still 75% of the value measured after 4 hours. This suggests that zolmitriptan and/or its metabolites may bind to the melanin of the eye. Because there could be accumulation in melanin rich tissues over time, this raises the possibility that zolmitriptan could cause toxicity in these tissues after extended use. However, no effects on the retina related to treatment with zolmitriptan were noted in any of the toxicity studies including those conducted by the nasal route. Although no systematic monitoring of ophthalmologic function was undertaken in clinical trials, and no specific recommendations for ophthalmologic monitoring are offered, prescribers should be aware of the possibility of long-term ophthalmologic effects.

5.8 Laboratory Tests

No monitoring of specific laboratory tests is recommended.

5.9 Drug/Laboratory Test Interactions

Zolmitriptan is not known to interfere with commonly employed clinical laboratory tests.

6 ADVERSE REACTIONS

6.1 Clinical Studies Experience

Because clinical studies are conducted under widely varying conditions, adverse reaction rates observed in the clinical studies of a drug cannot be directly compared to rates in the clinical studies of another drug and may not reflect the rates observed in practice.

Serious cardiac reactions, including myocardial infarction, have occurred following the use of ZOMIG Tablets. These reactions are extremely rare and most have been reported in patients with risk factors predictive of CAD. Reactions reported, in association with triptans, have included coronary artery vasospasm, transient myocardial ischemia, myocardial infarction, ventricular tachycardia, and ventricular fibrillation [see Contraindications (4.1) and Warnings and Precautions (5.1)].

Incidence in Controlled Clinical Trials:

Among 464 adult patients treating single attacks with zolmitriptan nasal spray in a blinded placebo controlled trial, there was a low withdrawal rate related to adverse reactions: 5 mg (1.3%), and placebo (0.4%). None of the withdrawals were due to a serious reaction. One patient was withdrawn due to abnormal ECG changes from baseline that was incidentally found 23 days after the last dose of ZOMIG Nasal Spray. The most common adverse reactions in clinical trials for ZOMIG Nasal Spray were: unusual taste, paresthesia, hyperesthesia, and dizziness.

Table 1 lists the adverse reactions that occurred in ≥ 2% of the 236 patients in the 5 mg dose group of the controlled clinical trial.

Table 1: Adverse reactions with an incidence of ≥ 2% of patients in the zolmitriptan 5 mg nasal spray treatment group by body system and greater than placebo.
Body system and; adverse reaction | Placebo; (N=228) | 5.0 mg; (N=236)
Atypical Sensations
Hyperesthesia | 0% | 5%
Paraesthesia | 6% | 10%
Ear/Nose/Throat
Disorder/Discomfort of nasal cavity | 2% | 3%
Pain and Pressure Sensations
Pain Location Specified | 1% | 4%
Pain Throat | 1% | 4%
Tightness Throat | 1% | 2%
Digestive
Dry Mouth | 0% | 2%
Nausea | 1% | 4%
Neurological
Somnolence | 2% | 4%
Unusual Taste | 3% | 21%
Other
Asthenia | 1% | 3%

Adverse clinical reactions occurring in ≥ 1% and < 2% of patients in all attacks of the controlled clinical trial were pain abdominal, pressure throat, vomiting, headache, tightness chest, dysphagia, insomnia, palpitation and reaction aggravation.

The incidence of adverse reactions in controlled clinical trials was not affected by gender, weight, or age of the patients (18-39 vs. 40-65 years of age), or presence of aura. There were insufficient data to assess the impact of race on the incidence of adverse reactions.

Local Adverse Reactions:

Among 922 patients using the zolmitriptan nasal spray to treat 2311 attacks in the controlled clinical study who were exposed, across all doses (0.5 to 5 mg), approximately 3% noted local irritation or soreness at the site of administration. Adverse reactions of any kind, perceived in the nasopharynx (which may include systemic effects of triptans) were severe in about 1% of patients and approximately 60% resolved in 1 hour. Nasopharyngeal examinations, in a subset of patients participating in two long term trials of up to one year duration, failed to demonstrate any clinically significant changes with repeated use of ZOMIG Nasal Spray.

All nasopharyngeal adverse reactions with an incidence of ≥ 2% of patients in any zolmitriptan nasal spray dose groups are included in ADVERSE REACTIONS Table 1.

Other Adverse Reactions:

In the paragraphs that follow, the frequencies of less commonly reported adverse clinical reactions are presented. Because the reports include reactions observed in open and uncontrolled studies, the role of ZOMIG in their causation cannot be reliably determined. Furthermore, variability associated with adverse reaction reporting, the terminology used to describe adverse reactions, etc., limit the value of the quantitative frequency estimates provided. Reaction frequencies are calculated as the number of patients who used ZOMIG Nasal Spray and reported a reaction divided by the total number of patients exposed to ZOMIG Nasal Spray (n=3059). All reported reactions are included except those already listed in the previous table, those too general to be informative, and those not reasonably associated with the use of the drug. Reactions are further classified within body system categories and enumerated in order of decreasing frequency using the following definitions: infrequent adverse reactions are those occurring in 1/100 to 1/1,000 patients and rare adverse reactions are those occurring in fewer than 1/1,000 patients.

Body:

Infrequent: allergic reaction, back pain, chills, cyst, flu syndrome, infection, jaw pain, pressure other, jaw tightening, edema of the face, abnormal laboratory test, neck pain, neoplasm, and neck tightness, chest heaviness, chest pain, and chest pressure

Rare: cellulitis, fever, jaw pressure, and neck heaviness

Cardiovascular:

Infrequent: arrhythmias, hypertension, syncope, thrombophlebitis, and tachycardia

Rare: angina pectoris, bradycardia, atrial fibrillation, myocardial infarct, vasodilation, and vascular disorder

Digestive:

Infrequent: diarrhea, dyspepsia, tongue edema, gastrointestinal disorder, increased saliva, and thirst

Rare: increased appetite, colitis, constipation, eructation, gastritis, gastrointestinal carcinoma, gingivitis, hepatic neoplasia, intestinal obstruction, jaundice, sialadenitis, and stomatitis

Endocrine System:

Rare: hyperthyroidism and thyroid edema

Hemic:

Infrequent: cyanosis

Rare: ecchymosis, lymphadenopathy and leukopenia

Metabolic Nutritional:

Rare: increased weight, dehydration, and peripheral edema

Musculoskeletal:

Infrequent: arthralgia, joint disorder, and myalgia

Rare: bone pain, osteoporosis, tenosynovitis and twitching

Nervous System:

Infrequent: agitation, amnesia, anxiety, ataxia, abnormal coordination, confusion, depersonalization, depression, hypertonia, insomnia, nervousness, speech disorder, abnormal thinking, tremor, vertigo, and circumoral paresthesia

Rare: apathy, convulsions, abnormal dreams, euphoria, hypertonia, irritability, tardive dyskinesia, manic reaction, neuropathy, and psychosis

Respiratory:

Infrequent: bronchitis, increased cough, dyspnea, epistaxis, laryngeal edema, pharyngitis, rhinitis, sinusitis, throat discomfort, and voice alteration

Rare: hiccup, hyperventilation, laryngitis, pneumonia, increased sputum, and yawning

Skin:

Infrequent: pruritus, rash, skin disorder, and sweating

Rare: eczema, erythema, erythema multiform, hair disorder, and neoplasm

Special Senses:

Infrequent: amblyopia, disorder of lacrimation, ear pain, eye pain, parosmia and tinnitus

Rare: conjunctivitis, dry eye, photophobia, and visual field defect

Urogenital:

Infrequent: polyuria and menorrhagia

Rare: breast carcinoma, dysmenorrhea, metrorrhagia, breast neoplasm, unintended pregnancy, suspicious PAP smear, uterine disorder, enlarged uterine fibroids, fibrocytic breast, vaginitis, urogenital neoplasm, cystitis, urinary tract infection, kidney pain, pyelonephritis, urinary frequency, urine impaired, and urinary tract disorder

The adverse experience profile seen with ZOMIG Nasal Spray is similar to that seen with ZOMIG tablets and ZOMIG-ZMT tablets except for the occurrence of local adverse reactions from the nasal spray (see ZOMIG Tablet Prescribing Information).

6.2 Postmarketing Experience with ZOMIG Tablets

The following adverse reactions were identified during post approval use of ZOMIG. Because these reactions are reported voluntarily from a population of uncertain size, it is not always possible to reliably estimate their frequency or establish a causal relationship to drug exposure.

The following section enumerates potentially important adverse reactions that have occurred in clinical practice and which have been reported spontaneously to various surveillance systems. The reactions enumerated represent reports arising from both domestic and non-domestic use of oral zolmitriptan. The reactions enumerated include all except those already listed in the ADVERSE REACTIONS section above or those too general to be informative. Because the reports cite reactions reported spontaneously from worldwide postmarketing experience, frequency of reactions and the role of zolmitriptan in their causation cannot be reliably determined.

Cardiovascular:

Coronary artery vasospasm, transient myocardial ischemia, angina pectoris, and myocardial infarction.

Digestive:

Very rare gastrointestinal ischemic reactions including splenic infarction, ischemic colitis and gastrointestinal infarction or necrosis have been reported; these may present as bloody diarrhea or abdominal pain [see Warnings and Precautions (5.4)].

General:

As with other 5-HT1B/1D agonists, there have been very rare reports of anaphylaxis or anaphylactoid reactions in patients receiving ZOMIG. There have been rare reports of hypersensitivity reactions, including angioedema.

Serotonin syndrome has also been reported during the postmarketing period [see Warnings and Precautions (5.5)].

Neurological:

As with other acute migraine treatments including other 5HT1 agonists, there have been rare reports of headache.

7 DRUG INTERACTIONS

7.1 Ergot-containing drugs

Ergot-containing drugs have been reported to cause prolonged vasospastic reactions. Because there is a theoretical basis that these effects may be additive, use of ergotamine-containing or ergot-type medications (like dihydroergotamine or methysergide) and zolmitriptan within 24 hours of each other should be avoided [see Contraindications (4.5)].

7.2 MAO-A Inhibitors

MAO-A inhibitors increase the systemic exposure of zolmitriptan. Therefore, the use of zolmitriptan in patients receiving MAO-A inhibitors is contraindicated [see Clinical Pharmacology (12.4) and Contraindications (4.7)].

7.3 5-HT1B/1D agonists (e.g. triptans)

Concomitant use of other 5-HT1B/1D agonists within 24 hours of ZOMIG treatment is not recommended [see Contraindications (4.5)].

7.4 Cimetidine

Following administration of cimetidine, the half-life and AUC of zolmitriptan and its active metabolites were approximately doubled [see Clinical Pharmacology (12.4)].

7.5 Selective Serotonin Reuptake Inhibitors/Serotonin Norepinephrine Reuptake Inhibitors and Serotonin Syndrome

Cases of life-threatening serotonin syndrome have been reported during combined use of selective serotonin reuptake inhibitors (SSRIs) or serotonin norepinephrine reuptake inhibitors (SNRIs) and triptans [see Warnings and Precautions (5.5)].

8 USE IN SPECIFIC POPULATIONS

8.1 Pregnancy

Pregnancy Category C. There are no adequate and well controlled studies in pregnant women; therefore, zolmitriptan should be used during pregnancy only if the potential benefit justifies the potential risk to the fetus. In reproductive toxicity studies in rats and rabbits, oral administration of zolmitriptan to pregnant animals resulted in embryolethality and fetal abnormalities (malformations and variations) at clinically relevant exposures.

When zolmitriptan was administered to pregnant rats during the period of organogenesis at oral doses of 100, 400, and 1200 mg/kg/day (plasma exposures (AUCs) ≈280, 1100, and 5000 times the human AUC at the maximum recommended human dose (MRHD) of 10 mg/day, there was a dose-related increase in embryolethality. A no-effect dose for embryolethality was not established. When zolmitriptan was administered to pregnant rabbits during the period of organogenesis at oral doses of 3, 10, and 30 mg/kg/day (plasma AUCs ≈1, 11, and 42 times the human AUC at the MRHD), there were increases in embryolethality and in fetal malformations and variations. The no-effect dose for adverse effects on embryo-fetal development was associated with a plasma AUC similar to that in humans at the MRHD. When female rats were given zolmitriptan during gestation, parturition, and lactation at oral doses of 25, 100, and 400 mg/kg/day (plasma AUCs ≈70, 280, and 1100 times that in human at the MRHD), an increased incidence of hydronephrosis was found in the offspring. The no-effect dose was associated with a plasma AUC ≈280 times that in humans at the MRHD.

8.3 Nursing Mothers

It is not known whether zolmitriptan is excreted in human milk. Because many drugs are excreted in human milk, caution should be exercised when zolmitriptan is administered to a nursing woman. Lactating rats dosed with zolmitriptan had levels in milk equivalent to maternal plasma levels at 1 hour and 4 times higher than plasma levels at 4 hours.

8.4 Pediatric Use

Safety and effectiveness of ZOMIG in pediatric patients have not been established; therefore, ZOMIG is not recommended for use in patients under 18 years of age.

A single, multicenter, double-blind, randomized placebo-controlled, study was conducted to evaluate the efficacy of zolmitriptan 5 mg nasal spray in the acute treatment of migraine headache in 171 evaluable adolescent subjects 12 to 17 years of age. Efficacy was not established in that study.

Adverse reactions observed in this study were similar in nature and frequency to those reported in ZOMIG Nasal Spray adult clinical trials. The most commonly reported adverse reactions (≥ 2% and > placebo) were dysgeusia (7%), nasal discomfort (3%), dizziness (2%), nasal congestion (2%), nausea (2%), and throat irritation (2%).

ZOMIG Nasal Spray has not been studied in pediatric patients under 12 years of age.

In the postmarketing experience with triptans, including ZOMIG, there is a limited number of reports that describe pediatric patients who have experienced clinically serious adverse events; those that were reported are similar in nature to those reported rarely in adults.

8.5 Geriatric Use

Although the pharmacokinetic disposition of the drug in the elderly is similar to that seen in younger adults, there is no information about the safety and effectiveness of zolmitriptan in this population because patients over age 65 were excluded from the controlled clinical trials [see Clinical Pharmacology (12.3)].

8.6 Hepatic Impairment

The effect of hepatic disease on the pharmacokinetics of zolmitriptan nasal spray has not been evaluated. After oral administration, zolmitriptan exposure was increased in patients with severe hepatic impairment, and significant elevation in blood pressure was observed in some patients. Because of the similarity in exposure, zolmitriptan tablets and nasal spray should have similar dosage adjustments and should be administered with caution in subjects with liver disease, generally using doses less than 2.5 mg. Doses lower than 5 mg can only be achieved through the use of an oral formulation [see Dosage and Administration (2.2) and Clinical Pharmacology (12.3)].

9 DRUG ABUSE AND DEPENDENCE

The abuse potential of ZOMIG has not been assessed in clinical trials.

10 OVERDOSAGE

There is no experience with acute overdose. Clinical study subjects receiving single 50 mg oral doses of zolmitriptan commonly experienced sedation.

The elimination half-life of ZOMIG is 3 hours [see Clinical Pharmacology (12.1)] and therefore monitoring of patients after overdose with ZOMIG should continue for at least 15 hours or while symptoms or signs persist.

There is no specific antidote to zolmitriptan. In cases of severe intoxication, intensive care procedures are recommended, including establishing and maintaining a patent airway, ensuring adequate oxygenation and ventilation, and monitoring and support of the cardiovascular system.

It is unknown what effect hemodialysis or peritoneal dialysis has on the plasma concentrations of zolmitriptan.

11 DESCRIPTION

ZOMIG® (zolmitriptan) Nasal Spray contains zolmitriptan, which is a selective 5-hydroxytryptamine 1B/1D (5-HT1B/1D) receptor agonist. Zolmitriptan is chemically designated as (S)-4-[[3-[2-(dimethylamino)ethyl]-1H-indol-5-yl]methyl]-2-oxazolidinone and has the following chemical structure:

The empirical formula is C16H21N3O2, representing a molecular weight of 287.36. Zolmitriptan is a white to almost white powder that is readily soluble in water. ZOMIG Nasal Spray is supplied as a clear to pale yellow solution of zolmitriptan, buffered to a pH 5.0. Each ZOMIG Nasal Spray contains 5 mg of zolmitriptan in a 100-μL unit dose aqueous buffered solution containing citric acid, anhydrous, USP, disodium phosphate dodecahydrate USP and purified water USP.

ZOMIG Nasal Spray is hypertonic. The osmolarity of ZOMIG Nasal Spray 5 mg is 420 to 470 mOsmol.

12 CLINICAL PHARMACOLOGY

12.1 Mechanism of Action

Zolmitriptan binds with high affinity to human recombinant 5-HT1D and 5-HT1B receptors. Zolmitriptan exhibits modest affinity for 5-HT1A receptors, but has no significant affinity (as measured by radioligand binding assays) or pharmacological activity at 5-HT2, 5-HT3, 5-HT4, α1-, α2- or β1-adrenergic; H1, H2, histaminic; muscarinic; D1, or D2 receptors. The N-desmethyl metabolite also has high affinity for 5-HT1B/1D and modest affinity for 5-HT1A receptors.

Current theories proposed to explain the etiology of migraine headache suggest that symptoms are due to local cranial vasodilatation and/or to the release of sensory neuropeptides (vasoactive intestinal peptide, substance P and calcitonin gene-related peptide) through nerve endings in the trigeminal system. The therapeutic activity of zolmitriptan for the treatment of migraine headache can most likely be attributed to the agonist effects at the 5-HT1B/1D receptors on intracranial blood vessels (including the arterio-venous anastomoses) and sensory nerves of the trigeminal system which result in cranial vessel constriction and inhibition of pro-inflammatory neuropeptide release.

12.3 Pharmacokinetics

Absorption:

Zolmitriptan nasal spray is rapidly absorbed via the nasopharynx as detected in a Photon Emission Tomography (PET) study using ^11C zolmitriptan. Zolmitriptan was detected in plasma by 5 minutes and peak plasma concentration generally was achieved by 3 hours. The time at which maximum plasma concentrations were observed was similar after single (1 day) or multiple (4 day) nasal dosing. Plasma concentrations of zolmitriptan are sustained for 4 to 6 hours after dosing. Zolmitriptan displays linear kinetics after multiple doses of 2.5 mg, 5 mg, or 10 mg. The mean relative bioavailability of the nasal spray formulation is 102%, compared with the oral tablet.

Zolmitriptan and its active metabolite display dose proportionality after single or multiple dosing. Dose proportional increases in zolmitriptan and N-desmethyl metabolite Cmax and AUC were observed for 2.5 and 5 mg nasal spray doses. The pharmacokinetics for elimination of zolmitriptan and its active N-desmethyl metabolite are similar for all nasal spray dosages. The N-desmethyl metabolite is detected in plasma by 15 minutes and peak plasma concentration is generally achieved by 3 hours after administration.

Food has no significant effect on the bioavailability of zolmitriptan.

Distribution:

Plasma protein binding of zolmitriptan is 25% over the concentration range of 10-1000 ng/mL. The mean (±SD) apparent volume of distribution for zolmitriptan nasal spray formulation is 8.4±3.3 L/kg.

Metabolism:

Zolmitriptan is converted to an active N-desmethyl metabolite such that the metabolite concentrations are about two-thirds that of zolmitriptan. Because the 5HT1B/1D potency of the metabolite is 2 to 6 times that of the parent compound, the metabolite may contribute a substantial portion of the overall effect after zolmitriptan administration.

Excretion:

The mean elimination half-life for zolmitriptan and its active N-desmethyl metabolite following nasal spray administration are approximately 3 hours, which is similar to the half-life values seen after oral tablet administration. The half-life values were similar for zolmitriptan and the N-desmethyl metabolite after single (1 day) and multiple (4 day) nasal dosing.

Mean total plasma clearance is 25.9 mL/min/kg, of which one-sixth is renal clearance. The renal clearance is greater than the glomerular filtration rate suggesting renal tubular secretion.

Special Populations:

Age:

The pharmacokinetics of oral zolmitriptan in healthy elderly non-migraineur volunteers (age 65 - 76 yrs) was similar to those in younger non-migraineur volunteers (age 18-39 yrs).

Gender:

Mean plasma concentrations of orally administered zolmitriptan were up to 1.5-fold higher in females than males.

Renal Impairment:

The effect of renal impairment on the pharmacokinetics of zolmitriptan nasal spray has not been evaluated. After orally dosing zolmitriptan, renal clearance was reduced by 25% in patients with severe renal impairment (Clcr ≥ 5 ≤ 25 mL/min) compared with the normal group (Clcr ≥ 70 mL/min); no significant change in renal clearance was observed in the moderately renally impaired group (Clcr ≥ 26 ≤ 50 mL/min).

Hepatic Impairment:

The effect of hepatic disease on the pharmacokinetics of zolmitriptan nasal spray has not been evaluated. In severely hepatically impaired patients, the mean Cmax, Tmax, and AUC0-∞ of zolmitriptan dosed orally were increased 1.5, 2, and 3-fold, respectively, compared with normals. Seven out of 27 patients experienced 20 to 80 mm Hg elevations in systolic and/or diastolic blood pressure after a 10 mg dose. Because of the similarity in exposure, zolmitriptan tablets and nasal spray should have similar dosage adjustments and should be administered with caution in subjects with liver disease, generally using doses less than 2.5 mg. Doses lower than 5 mg can only be achieved through the use of an oral formulation [see Dosing and Administration (2.2) and Use in Special Populations (8.6) ].

Hypertensive Patients:

No differences in the pharmacokinetics of oral zolmitriptan or its effects on blood pressure were seen in mild to moderate hypertensive volunteers compared with normotensive controls.

Race:

Retrospective analysis of pharmacokinetic data between Japanese and Caucasians revealed no significant differences for orally dosed zolmitriptan.

12.4 Drug Interactions

All drug interaction studies were performed in healthy volunteers using a single 10 mg dose of zolmitriptan and a single dose of the other drug except where otherwise noted. Eight drug interaction studies have been performed with zolmitriptan tablets and one study (xylometazoline) was performed with nasal spray.

Xylometazoline:

An in vivo drug interaction study with ZOMIG Nasal Spray indicated that 1 spray (100μL dose) of xylometazoline (0.1% w/v), a decongestant, administered 30 minutes prior to a 5 mg nasal dose of zolmitriptan did not alter the pharmacokinetics of zolmitriptan.

Fluoxetine:

The pharmacokinetics of zolmitriptan, as well as its effect on blood pressure, were unaffected by 4 weeks of pre-treatment with oral fluoxetine (20 mg/day).

MAO Inhibitors:

Following one week of administration of 150 mg bid moclobemide, a specific MAO-A inhibitor, there was an increase of about 25% in both Cmax and AUC for zolmitriptan and a 3-fold increase in the Cmax and AUC of the active N-desmethyl metabolite of zolmitriptan [see Contraindications (4) and Warnings and Precautions (5)].

Selegiline, a selective MAO-B inhibitor, at a dose of 10 mg/day for 1 week, had no effect on the pharmacokinetics of zolmitriptan and its metabolite.

Propranolol:

Cmax and AUC of zolmitriptan increased 1.5-fold after one week of dosing with propranolol (160 mg/day). Cmax and AUC of the N-desmethyl metabolite were reduced by 30% and 15%, respectively. There were no interactive effects on blood pressure or pulse rate following administration of propranolol with zolmitriptan.

Acetaminophen:

A single 1 g dose of acetaminophen does not alter the pharmacokinetics of zolmitriptan and its N-desmethyl metabolite. However, zolmitriptan delayed the Tmax of acetaminophen by one hour.

Metoclopramide:

A single 10 mg dose of metoclopramide had no effect on the pharmacokinetics of zolmitriptan or its metabolites.

Oral Contraceptives:

Retrospective analysis of pharmacokinetic data across studies indicated that mean plasma concentrations of zolmitriptan were generally higher in females taking oral contraceptives compared with those not taking oral contraceptives. Mean Cmax and AUC of zolmitriptan were found to be higher by 30% and 50%, respectively, and Tmax was delayed by one-half hour in females taking oral contraceptives. The effect of zolmitriptan on the pharmacokinetics of oral contraceptives has not been studied.

Cimetidine:

Following the administration of cimetidine, the half-life and AUC of a 5 mg dose of zolmitriptan and its active metabolite were approximately doubled [see Drug Interactions (7.4)].

13 NONCLINICAL TOXICOLOGY

13.1 Carcinogenesis, Mutagenesis, Impairment of Fertility

Carcinogenesis

Zolmitriptan was administered to mice and rats at doses up to 400 mg/kg/day. Mice were dosed for 85 weeks (males) and 92 weeks (females); rats were dosed for 101 weeks (males) and 86 weeks (females). There was no evidence of drug-induced tumors in mice at plasma exposures (AUC) up to approximately 700 times that in humans at the maximum recommended human dose (MRHD) of 10 mg/day. In rats, there was an increase in the incidence of thyroid follicular cell hyperplasia and thyroid follicular cell adenomas seen in male rats receiving 400 mg/kg/day. The no-effect dose for tumors in rats (100 mg/kg/day) was associated with a plasma AUC ≈700 times that in humans at the MRHD.

13.2 Animal Toxicology and/or Pharmacology

Zolmitriptan was positive in an in vitro bacterial reverse mutation (Ames) assay and in an in vitro chromosomal aberration assay in human lymphocytes. Zolmitriptan was negative in an in vitro mammalian gene cell mutation (CHO/HGPRT) assay and in oral in vivo micronucleus assays in mouse and rat.

13.3 Impairment of Fertility

Studies of male and female rats administered zolmitriptan prior to and during mating and up to implantation showed no impairment of fertility at oral doses up to 400 mg/kg/day. The plasma exposure (AUC) at this dose was approximately 3000 times that in humans at the maximum recommended human dose of 10 mg/day.

14 CLINICAL STUDIES

The efficacy of ZOMIG Nasal Spray 5 mg in the acute treatment of migraine headache with or without aura was demonstrated in a randomized, outpatient, double-blind, placebo-controlled trial.

Patients were instructed to treat a moderate to severe headache. Headache response, defined as a reduction in headache severity from moderate or severe pain to mild or no pain, was assessed 15, 30, 45 minutes and 1, 2, and 4 hours after dosing. Pain free response rates and associated symptoms such as nausea, photophobia, and phonophobia were also assessed. A dose of escape medication was allowed 4 to 24 hours after the initial treatment for persistent and recurrent headache.

Of the 1372 patients treated in the study, 83% were female and 99% were Caucasian, with a mean age of 40.6 years (range 18 to 65 years).

The two hour headache response rates in patients treated with ZOMIG Nasal Spray were statistically significant among patients receiving ZOMIG Nasal Spray compared with placebo. There was a greater percentage of patients with a headache response at 2 hours in the higher dose groups. The headache response efficacy endpoints of the controlled clinical study, analyzed from the first attack data, are shown in Table 2.

Table 2: First Attack Data: Percentage of Patients with Headache Response to ZOMIG Nasal Spray (Mild or No Headache) 2 Hours Following Treatment

(N = number of randomized patients treating a migraine attack). The 2 hour headache response wNas the primary end-point.

N | PLACEBO (226) | ZOMIG 5 mg (235)
2 hours | 31% | 69% [p <0.0001 in comparison with placebo]

The estimated probability of achieving an initial headache response by 4 hours following treatment with ZOMIG Nasal Spray is depicted in Figure 1.

Note:

Figure 1 shows the Kaplan-Meier plot of the probability over time of obtaining headache response (moderate or severe headache improving to mild or no pain) following treatment with zolmitriptan nasal spray. The averages displayed are based on a placebo controlled, outpatient trial providing evidence of efficacy. Patients not achieving headache response or taking additional treatment prior to 4 hours were censored to 4 hours.

For patients with migraine associated photophobia, phonophobia, and nausea at baseline, there was a decreased incidence of these symptoms following administration of ZOMIG Nasal Spray as compared with placebo.

Four to 24 hours following the initial dose of study treatment, patients were allowed to use additional treatment for pain relief in the form of a second dose of study treatment or other medication. The estimated probability of patients taking a second dose or other medication for migraine over the 24 hours following the initial dose of study treatment is summarized in Figure 2.

*This Kaplan-Meier plot is based on data obtained from the placebo controlled clinical trial. Patients not using additional treatments were censored at 24 hours. The plot includes both patients who had headache response at 2 hours and those who had no response to the initial dose. It should be noted that the protocol did not allow remedication within 4 hours post dose.

The efficacy of ZOMIG was unaffected by presence of aura; presence of headache upon awakening, relationship to menses; gender, age or weight of the patient; or presence of pre-treatment nausea.

The efficacy of ZOMIG Nasal Spray 5 mg was further supported by an interim analysis of another similarly designed trial. The 2 hour headache response rates for the first 210 subjects in that study for ZOMIG 5 mg and placebo were 70% and 47%, respectively (N=108 and 102, respectively, p=0.0006).

16 HOW SUPPLIED/STORAGE AND HANDLING

The ZOMIG Nasal Spray device is a blue colored plastic device with a gray protection cap, labeled to indicate the nominal dose. Each ZOMIG Nasal Spray device administers a single dose of ZOMIG.

ZOMIG Nasal Spray is supplied as a clear to pale yellow solution of zolmitriptan, buffered to a pH 5.0. Each ZOMIG Nasal Spray device contains 5 mg of zolmitriptan in a 100-μL unit dose aqueous buffered solution containing citric acid, anhydrous, USP, disodium phosphate dodecahydrate USP and purified water USP.

5 mg ZOMIG® Nasal Spray is supplied in boxes of 6 single use nasal spray units. (NDC 21695-955-06).

Each ZOMIG® Nasal Spray single dose unit spray supplies 5 mg of zolmitriptan. The ZOMIG® Nasal Spray unit must be discarded after use.

Store at controlled room temperature, 20-25°C (68-77°F) [see USP].

17 PATIENT COUNSELING INFORMATION

See FDA-Approved Patient Labeling (17.5)

17.1 Risk of Myocardial Ischemia and/or Infarction, Other Adverse Cardiac Events, Other Vasospasm-related Event, and Cerebrovascular Events

Patients should be informed that ZOMIG may cause serious cardiovascular side effects such as myocardial infarction or stroke, which may result in hospitalization and even death. Although serious cardiovascular events can occur without warning symptoms, patients should be alert for the signs and symptoms of chest pain, shortness of breath, weakness, slurring of speech, and should ask for medical advice when observing any indicative sign or symptoms. Patients should be apprised of the importance of this follow-up [see Warnings and Precautions (5.1, 5.3, 5.4)].

17.2 Serotonin Syndrome

Patients should be cautioned about the risk of serotonin syndrome with the use of ZOMIG or other triptans, particularly during combined use with selective serotonin reuptake inhibitors (SSRIs) or serotonin norepinephrine reuptake inhibitors (SNRIs) [see Warnings and Precautions (5.5)].

17.3 Device Use

The ZOMIG Nasal Spray device is packaged in a carton and is a blue colored plastic device with a gray protection cap, labeled to indicate the nominal dose. Patients should be cautioned to not remove the gray protection cap until prior to dosing. The ZOMIG Nasal Spray device is placed in a nostril and actuated to deliver a single dose. Patients should be cautioned to avoid spraying the contents of the device in their eyes.

17.4 Pregnancy

ZOMIG should not be used during pregnancy unless the potential benefit justifies the potential risk to the fetus.

17.5 Approved Patient Labeling

Please read this information before you start taking ZOMIG Nasal Spray and each time you renew your prescription just in case anything has changed. Remember, this summary does not take the place of discussions with your doctor. You and your doctor should discuss ZOMIG Nasal Spray when you start taking your medication and at regular checkups.

What is ZOMIG Nasal Spray?

ZOMIG Nasal Spray is a prescription medication used to treat migraine headaches in adults. ZOMIG Nasal Spray is not for other types of headaches. The safety and efficacy of ZOMIG in patients under 18 have not been established.

What is a Migraine Headache?

Migraine is an intense, throbbing headache. You may have pain on one or both sides of your head. You may have nausea and vomiting, and be sensitive to light and noise. The pain and symptoms of a migraine headache can be worse than a common headache. Some women get migraines around the time of their menstrual period. Some people have visual symptoms before the headache, such as flashing lights or wavy lines, called an aura.

How does ZOMIG Nasal Spray work?

Treatment with ZOMIG Nasal Spray reduces swelling of blood vessels surrounding the brain. This swelling is associated with the headache pain of a migraine attack. ZOMIG Nasal Spray blocks the release of substances from nerve endings that cause more pain and other symptoms like nausea, and sensitivity to light and sound. It is thought that these actions contribute to relief of your symptoms by ZOMIG Nasal Spray.

Who should not take ZOMIG Nasal Spray?

Do not take ZOMIG Nasal Spray if you:

Have heart disease or a history of heart disease
Have uncontrolled high blood pressure
Have hemiplegic or basilar migraine (if you are not sure about this, ask your doctor)
Have or had a stroke or problems with your blood circulation
Have serious liver problems
Have taken any of the following medicines in the last 24 hours: other “triptans” like almotriptan (AXERT®), eletriptan (RELPAX®), frovatriptan (FROVA®), naratriptan (AMERGE®), rizatriptan (MAXALT®), sumatriptan (IMITREX®), sumatriptan/naproxen (TREXIMET); ergotamines like BELLERGAL-S®, CAFERGOT®, ERGOMAR®, WIGRAINE®; dihydroergotamine like D.H.E. 45® or MIGRANAL®; or methysergide (SANSERT®). These medications have side effects similar to ZOMIG Nasal Spray.
Have taken monoamine oxidase (MAO) inhibitors such as phenelzine sulfate (NARDIL®) or tranylcypromine sulfate (PARNATE®) for depression or other conditions, or if it has been less than 2 weeks since you stopped taking a MAO inhibitor.
Are allergic to ZOMIG Nasal Spray or any of its ingredients. The active ingredient is zolmitriptan. The inactive ingredients are listed at the end of this leaflet.

Tell your doctor about all the medicines you take or plan to take, including prescription and nonprescription medicines, supplements, and herbal remedies.

Tell your doctor if you are taking selective serotonin reuptake inhibitors (SSRIs) or serotonin norepinephrine reuptake inhibitors (SNRIs), two types of drugs for depression or other disorders. Common SSRIs are CELEXA® (citalopram HBr), LEXAPRO® (escitalopram oxalate), PAXIL® (paroxetine), PROZAC® (fluoxetine), SYMBYAX® (olanzapine/fluoxetine), ZOLOFT® (sertraline), SARAFEM® (fluoxetine) and LUVOX® (fluvoxamine). Common SNRIs are CYMBALTA® (duloxetine) and EFFEXOR® (venlafaxine). Your doctor will decide if you can take ZOMIG Nasal Spray with your other medicines.

Tell your doctor if you know that you have any of the following: risk factors for heart disease like high cholesterol, diabetes, smoking, obesity (overweight), menopause, or a family history of heart disease or stroke.

Tell your doctor if you are pregnant, planning to become pregnant, breast feeding, planning to breast feed, or not using effective birth control.

How should I take ZOMIG NASAL Spray?

The ZOMIG Nasal Spray device is a blue colored plastic sprayer device with a gray protection cap, labeled to indicate the dose. For adults, the usual dose is a single nasal spray taken into one nostril. If your headache comes back after your first dose, you may take a second dose anytime after 2 hours of taking the first dose. For any attack where the first dose didn’t work, do not take a second dose without talking with your doctor. Do not take more than a total of 10 mg of ZOMIG (tablets or spray combined) in any 24-hour period. If you take too much medicine, contact your doctor, hospital emergency department, or poison control center right away.

The ZOMIG Nasal Spray device consists of the following parts:

A. The Tip: This is the part that you put into your nostril. The medicine comes out of a tiny hole in the top.

B. The Protective Cap: This covers the tip to protect it. Do not remove the protective cap until just before you are ready to take your ZOMIG Nasal Spray.

C. The Finger-grip: This is the part that you hold when you use the sprayer.

D. The Plunger: This is the part that you press when you put the tip into your nostril. This sprayer works only once.

Steps for using ZOMIG Nasal Spray (Please read all steps before using for the first time):

1. Blow your nose gently before use. Remove the protective cap (B) (Figure 1). Hold the nasal sprayer device gently with your fingers and thumb as shown in the picture to the right (Figure 2). There is only one dose in the nasal sprayer. Do not try to prime the nasal sprayer or you will lose the dose. Do not press the plunger until you have put the tip into your nostril or you will lose the dose.

2. Block one nostril by pressing firmly on the side of your nose (Figure 3). Either nostril can be used. Put the tip (A) of the sprayer device into the other nostril as far as feels comfortable and tilt your head slightly as shown in the picture to the right (Figure 4).

Do not press the plunger yet.

Do not spray the contents of the device in your eyes.

3. Breathe in gently through your nose and at the same time press the plunger (D) firmly with your thumb. The plunger may feel stiff and you may hear a click. Keep your head slightly tilted back and remove the tip from your nose. Breathe gently through your mouth for 5-10 seconds. You may feel liquid in your nose or the back of your throat. This is normal and will soon pass.

What are the possible side effects of ZOMIG Nasal Spray?

ZOMIG Nasal Spray is generally well tolerated. As with any medicine, people taking ZOMIG Nasal Spray may have side effects. The side effects are usually mild and do not last long.

The most common side effects of ZOMIG Nasal Spray are:

unusual taste, dry mouth
tingling sensation, skin sensitivity, especially around the nose
pain, pressure, and tightness sensations (eg, in the nose, throat, or chest)
drowsiness, weakness, dizziness
nausea

In very rare cases, patients taking triptans may experience serious side effects, such as heart attacks, high blood pressure, stroke, or serious allergic reactions. Extremely rarely, patients have died. Call your doctor right away if you have any of the following problems after taking ZOMIG Nasal Spray:

severe tightness, pain, pressure or heaviness in your chest, throat, neck, or jaw
shortness of breath or wheezing
sudden or severe stomach pain
hives; tongue, mouth, or throat swelling
problems seeing
unusual weakness or numbness

Some people may have a reaction called serotonin syndrome, which can be life-threatening, when they use ZOMIG. In particular, this reaction may occur when they use ZOMIG together with certain types of antidepressants known as SSRIs or SNRIs. Symptoms may include mental changes (hallucinations, agitation, coma), fast heartbeat, changes in blood pressure, high body temperature or sweating, tight muscles, trouble walking, nausea, vomiting, and diarrhea. Call your doctor immediately if you have any of these symptoms after taking ZOMIG.

This is not a complete list of side effects. Talk to your doctor if you develop any symptoms that concern you.

What to do in case of an overdose?

Call your doctor or poison control center or go to the ER.

General advice about ZOMIG Nasal Spray

Medicines are sometimes prescribed for conditions that are not mentioned in patient information leaflets. Do not use ZOMIG Nasal Spray for a condition for which it was not prescribed. Do not give ZOMIG Nasal Spray to other people, even if they have the same symptoms as you. People may be harmed if they take medicines that have not been prescribed for them.

This leaflet summarizes the most important information about ZOMIG Nasal Spray. If you would like more information about ZOMIG Nasal Spray, talk to your doctor. You can ask your doctor or pharmacist for information on ZOMIG Nasal Spray that is written for health professionals. You can also call 1-800-236-9933 or visit our web site at www.ZOMIG.com.

What are the Ingredients in ZOMIG Nasal Spray?

Active ingredient: zolmitriptan

Inactive ingredients: anhydrous citric acid, dibasic sodium phosphate, and purified water

Store your medication at controlled room temperature, 20-25°C (68-77°F), and away from children. Discard after use or when it expires.

ZOMIG is a registered trademark of the AstraZeneca group of companies.

Other brands mentioned are trademarks of their respective owners and are not trademarks of the AstraZeneca group of companies. The makers of these brands are not affiliated with AstraZeneca or its products.

©AstraZeneca 2008

Manufactured for:

AstraZeneca Pharmaceuticals LP

Wilmington, Delaware 19850

By: AstraZeneca UK Limited, Macclesfield,

Cheshire UK

Made in the United Kingdom

31455–00

Repackaged by:

Rebel Distributors Corp

Thousand Oaks, CA 91320